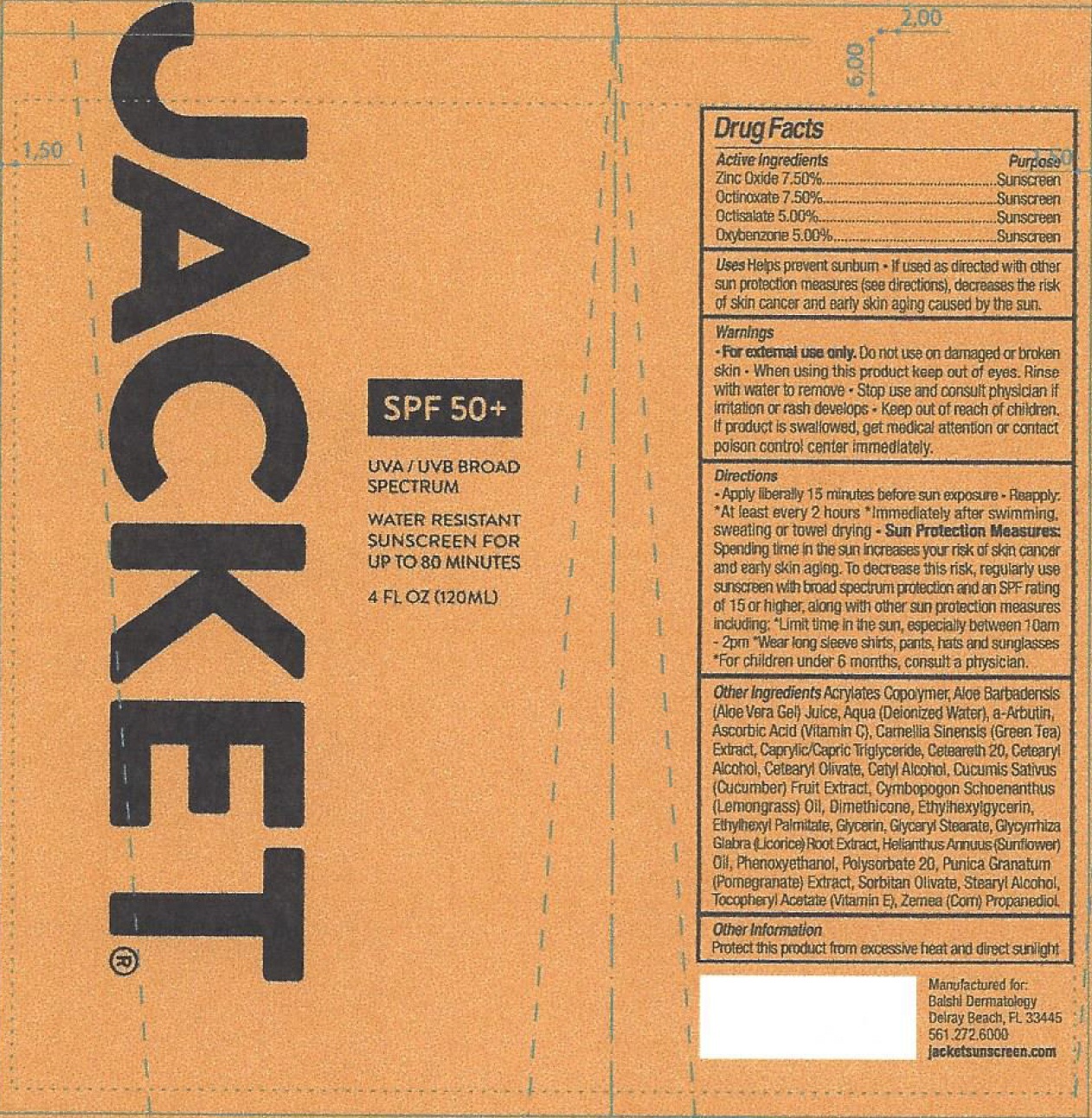 DRUG LABEL: JACKET SPF 50
NDC: 71070-768 | Form: CREAM
Manufacturer: Balshi MD Dermaceuticals
Category: otc | Type: HUMAN OTC DRUG LABEL
Date: 20231105

ACTIVE INGREDIENTS: ZINC OXIDE 75 mg/1 g; OCTINOXATE 75 mg/1 g; OCTISALATE 50 mg/1 g; OXYBENZONE 50 mg/1 g
INACTIVE INGREDIENTS: ALOE VERA LEAF; WATER; ARBUTIN; ASCORBIC ACID; GREEN TEA LEAF; MEDIUM-CHAIN TRIGLYCERIDES; POLYOXYL 20 CETOSTEARYL ETHER; CETOSTEARYL ALCOHOL; CETEARYL OLIVATE; CUCUMBER; CYMBOPOGON SCHOENANTHUS OIL; DIMETHICONE; ETHYLHEXYLGLYCERIN; ETHYLHEXYL PALMITATE; GLYCERIN; GLYCERYL MONOSTEARATE; GLYCYRRHIZA GLABRA; HELIANTHUS ANNUUS FLOWERING TOP; PHENOXYETHANOL; POLYSORBATE 20; POMEGRANATE; SORBITAN OLIVATE; STEARYL ALCOHOL; .ALPHA.-TOCOPHEROL; CORN; PROPANEDIOL

JACKET SPF 50+ CREAM

Active Ingredients

Zinc Oxide 7.50%

Octinoxate 7.50%

Octisalate 5.00%

Oxybenzone 5.00%

Purpose

Sunscreen

Uses

Helps prevent sunburn

- If used as directed with other sun protection measures (see directions), decreases the risk of skin cancer and early skin aging caused by the sun.

Warnings

- For external use only.

Do not use

on damaged or broken skin

When using this product

keep out of eyes. Rinse with water to remove

Stop use and consult physician if

irritation or rash develops

Keep out if reach of children.

If product is swallowed, get medical attention or contact poison control center immediately.

Directions

- Apply liberally 15 minutes before sun exposure • Reapply: • At least every 2 hours • Immediately after swimming, sweating or towel drying
- Spending time in the sun increases your risk of skin cancer and early skin aging. To decrease this risk, regularly use sunscreen with broad spectrum protection and an SPF rating of 15 or higher, along with other sun protection measures including: Sun Protection Measures:
- Limit time in the sun, especially between 10am -2pm
- Wear long sleeve shirts, pants, hats and sunglasses
- For children under 6 months, consult a physician.

Other Ingredients

Acrylates Copolymer, Aloe Barbadensis (Aloe Vera Gel) Juice, Aqua (Deionized Water), A-Arbutin, Ascorbic Acid (Vitamin C), Camellia Sinensis (Green Tea) Extract, Caprylic/Capric Triglyceride, Ceteareth 20, Cetearyl Alcohol, Cetearyl Olivate, Cetyl Alcohol Cucumis Sativus (Cucumber) Fruit Extract, Cymbopogon Schoenanthus (Lemongrass) Oil, Dimethicone, Ethylhexylgycerin, Ethylhexyl Palmitate, Glycerin, Glyceryl Stearate, Glycyrrhiza Glabra (Licorice) Root Extract, Helianthus Annuus (Sunflower) Oil, Phenoxyethanol, Polysorbate 20, Punica Granatum (Pomegranate) Extract, Sorbitan Olivate, Stearyl Alcohol, Tocopheyl Acetate (Vitamin E), Zema (Corn), Propanediol